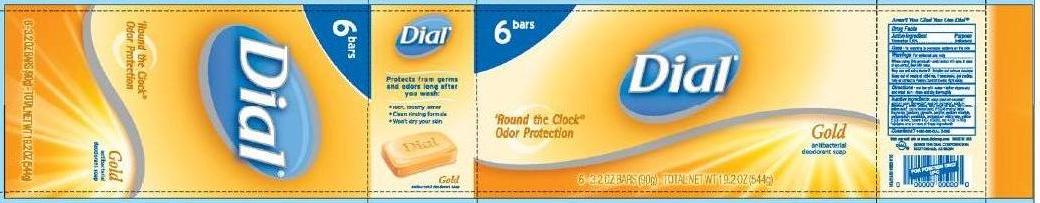 DRUG LABEL: Dial Gold Bar
NDC: 10889-100 | Form: SOAP
Manufacturer: VVF Kansas Services LLC
Category: otc | Type: HUMAN OTC DRUG LABEL
Date: 20090901

ACTIVE INGREDIENTS: triclocarban 0.60 1/1 1

Dial Antibacterial Deodorant Soap Gold Bar(triclocarban)

ACTIVE INGREDIENT

Triclocarban 0.60%

PURPOSE

Antibacterial

USES

For washing to decrease bacteria on the skin

WARNINGS

For external use only.

When using this product - avoid contact with eyes. In case of eye contact, flush with water.

Stop use and ask doctor if - irritation and redness develops

Keep out of reach of children. If swallowed, get medical help or contact a Poison Control Center right away.

DIRECTIONS

- Wet bar with water
- Later vigorously and wash skin
- Rinse and dry thoroughly

INACTIVE INGREDIENTS

soap (sodium cocate*, sodium palm kernelate*, sodium palmate*, sodium tallowate*), water (aqua), talc, coconut acid*, palm acid*, tallow acid*, palm kernel acid, PEG-6 methyl ether, fragrance (parfum), glycerin, sorbitol, sodium chloride, pentasodium pentetate, tetrasodium etidronate, yellow 5 (Cl 19140), yellow 8 (Cl 45350) red 4 (Cl 14700)

*contains one or more of these ingredients

QUESTIONS?

1-800-258-DIAL (3425)

PRODUCT PACKAGING

Dial 'Round the Clock(R) Odor Protection

Gold anitbacterial deodorant soap

6 - 3.2 OZ BARS (90g) - TOTAL NET WT 19.2 OZ (544g)

Protects from germs and odors long after you wash:

- Rich, creamy lather
- Clean rinsing formula
- Won't dry your skin

Visit our web site at www.dialsoap.com MADE IN USA
(C) 2008 THE DIAL CORPORATION
SCOTTSDALE, AZ 85254